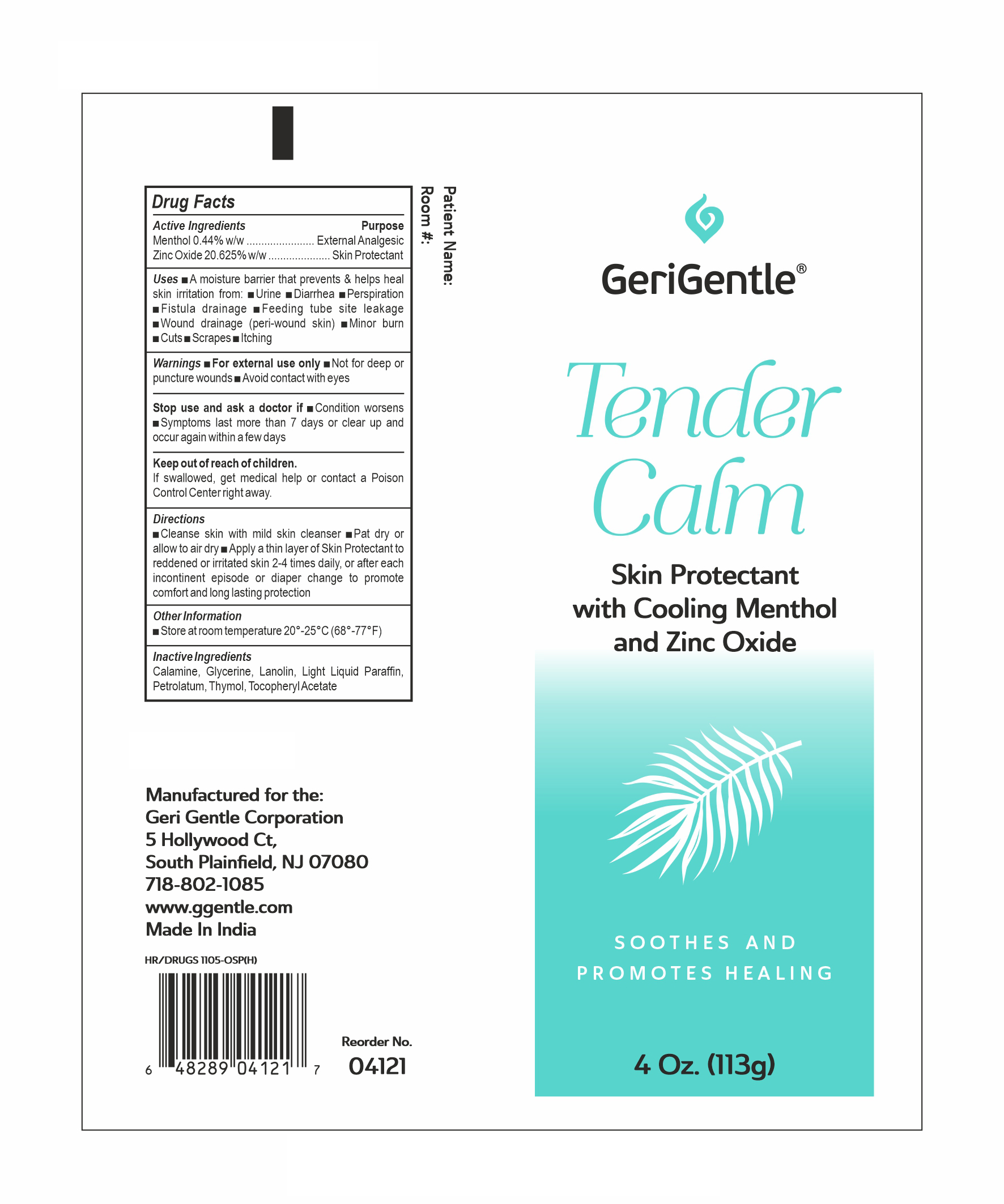 DRUG LABEL: Menthol and Zinc Oxide
NDC: 69771-013 | Form: OINTMENT
Manufacturer: GERI-GENTLE CORPORATION
Category: otc | Type: HUMAN OTC DRUG LABEL
Date: 20250106

ACTIVE INGREDIENTS: MENTHOL 0.44 g/100 g; ZINC OXIDE 20.625 g/100 g
INACTIVE INGREDIENTS: GLYCERIN; FERRIC OXIDE RED; LANOLIN; LIGHT MINERAL OIL; .ALPHA.-TOCOPHEROL ACETATE; THYMOL; PETROLATUM

GG Tender Calm
Menthol 0.44% w/w…………….……External Analgesic
Zinc Oxide 20.625% w/w………………. Skin Protectant

Active Ingredients

Menthol 0.44% w/w

Zinc Oxide 20.625% w/w

Purpose

Menthol 0.44% w/w…………….……External Analgesic

Zinc Oxide 20.625% w/w………………. Skin Protectant

uses

A moisture barrier that prevents and helps heal skin irritations from;

- urine
- diarrhea
- perspiration
- fistula drainage
- feeding tube site leakage
- wound drainage (peri-wound skin)
- minor burns
- cuts
- scrapes
- itching

Warnings:

■For external use only ■Not for deep or puncture wounds ■Avoid contact with eyes

Stop use and ask a doctor if

■Condition worsens

■Symptoms last more than 7 days or clear up and occur again within a few days

Keep Out Of Reach Of Children

If swallowed , get medical help or contact a Poison Control Center right away.

Dosage & Administration:

- Clean skin with mild skin cleanser
- Pat dry or allow to air dry
- Apply a thin layer of Calasoothe to reddened or irritated skin 2-4 times daily, or after each incontinent episode or diaper change to promote comfort and long lasting protection

Inactive Ingredients

Calamine, Glycerine, Lanolin, Light Liquid Parafﬁn, Petrolatum, Thymol, Tocopheryl Acetate